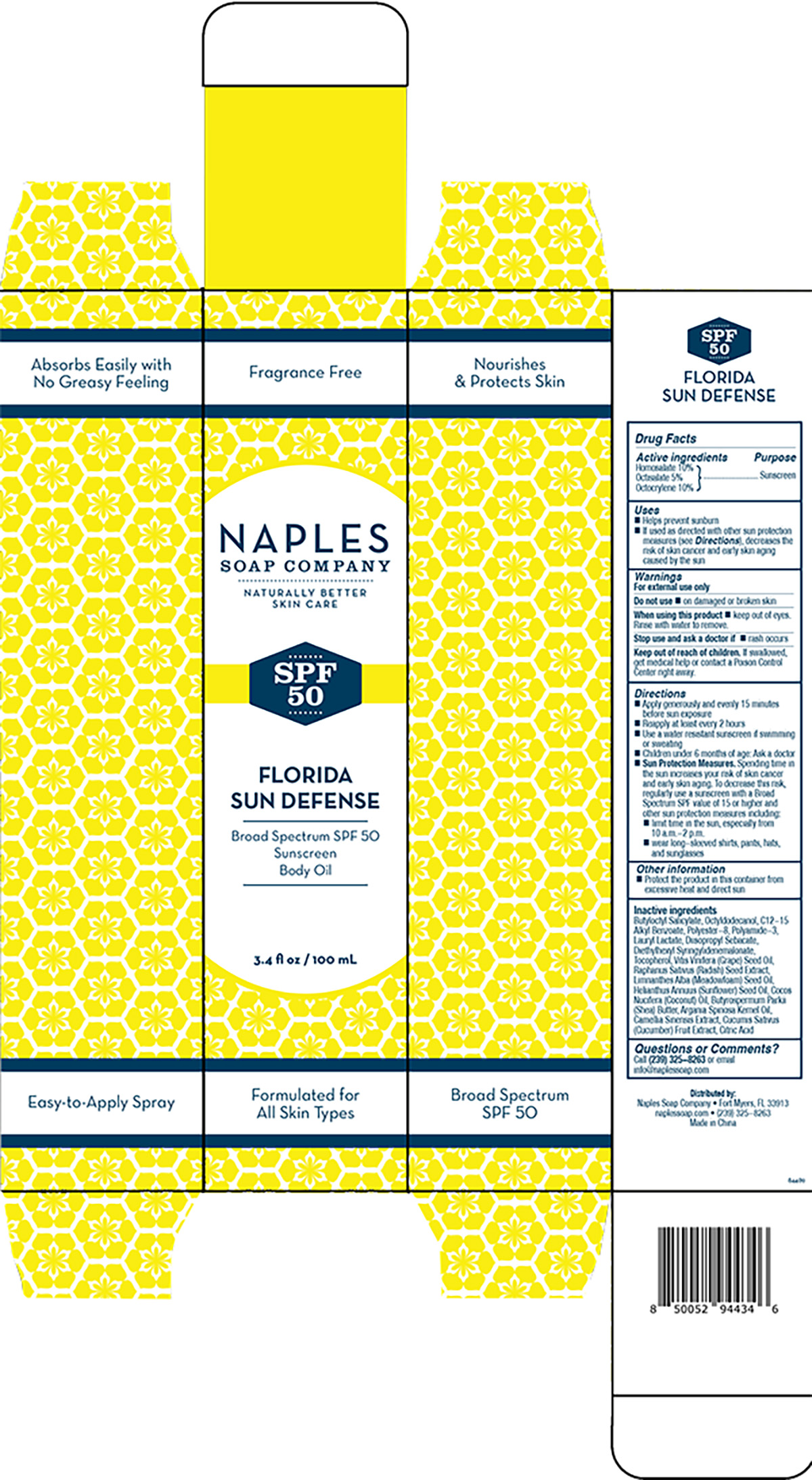 DRUG LABEL: SPF 50 Florida Sun Defense
NDC: 84489-100 | Form: OIL
Manufacturer: Naples Soap Company, Inc.
Category: otc | Type: HUMAN OTC DRUG LABEL
Date: 20260106

ACTIVE INGREDIENTS: OCTOCRYLENE 10 g/100 mL; HOMOSALATE 10 g/100 mL; OCTISALATE 5 g/100 mL
INACTIVE INGREDIENTS: POLYAMIDE-3 (20000 MW); OCTYLDODECANOL; BUTYROSPERMUM PARKII (SHEA) BUTTER; LAURYL LACTATE; DIETHYLHEXYL SYRINGYLIDENEMALONATE; GRAPE SEED OIL; LIMNANTHES ALBA (MEADOWFOAM) SEED OIL; HELIANTHUS ANNUUS (SUNFLOWER) SEED OIL; BUTYLOCTYL SALICYLATE; POLYESTER-8 (1400 MW, CYANODIPHENYLPROPENOYL CAPPED); CUCUMBER; CITRIC ACID; C12-15 ALKYL BENZOATE; DIISOPROPYL SEBACATE; TOCOPHEROL; RAPHANUS SATIVUS VAR. SATIVUS SEED; COCOS NUCIFERA (COCONUT) OIL; ARGANIA SPINOSA KERNEL OIL; CAMELLIA SINENSIS WHOLE

Drug Facts

Active ingredients

Homosalate 10%

Octisalate 5%

Octocrylene 10%

Purpose

Sunscreen

Uses

- Helps prevent sunburn
- lf used as directed with other sun protection measures (see Directions), decreases the risk of skin cancer and early skin aging caused by the sun

Warnings

For external use only

Do not use

- on damaged or broken skin

When using this product

- keep out of eyes. Rinse with water to remove.

Stop use and ask a doctor if

- rash occurs

Keep out of reach of children. If swallowed, get medical help or contact a Poison Control Center right away.

Directions

- Apply generously and evenly 15 minutes before sun exposure
- Reapply at least every 2 hours
- Use a water resistant sunscreen if swimming or sweating
- Children under 6 months of age: Ask a doctor
- Sun Protection Measures. Spending time in the sun increases your risk of skin cancer and early skin aging. To decrease this risk, regularly use a sunscreen with a Broad Spectrum SPF value of 15 or higher and other sun protection measures including:
- limit time in the sun, especially from 10 a.m.-2 p.m.
- wear long-sleeved shirts, pants, hats, and sunglasses

Other information

- Protect the product in this container from excessive heat and direct sun

Inactive ingredients

Butyloctyl Salicylate, Octyldodecanol, C12-15 Alkyl Benzoate, Polyester-8, Polyamide-3, Lauryl Lactate, Diisopropyl Sebacate, Diethylhexyl Syringylidenemalonate, Tocopherol, Vitis Vinifera (Grape) Seed Oil, Raphanus Sativus (Radish) Seed Extract, Limnanthes Alba (Meadowfoam) Seed Oil, Helianthus Annuus (Sunflower) Seed Oil, Cocos Nucifera (Coconut) Oil, Butyrospermum Parkii (Shea) Butter, Argania Spinosa Kernel Oil, Camellia Sinensis Extract, Cucumis Sativus (Cucumber) Fruit Extract, Citric Acid

Questions or Comments?

Call (239) 325-8263 or email info@naplessoap.com

PRINCIPAL DISPLAY PANEL - 100 ML CARTON LABEL

NAPLES

SOAP COMPANY

NATURALLY BETTER

SKIN CARE

SPF

50

FLORIDA

SUN DEFENSE

Broad Spectrum SPF 50

Sunscreen

Body Oil

3.4 fl oz / 100 mL